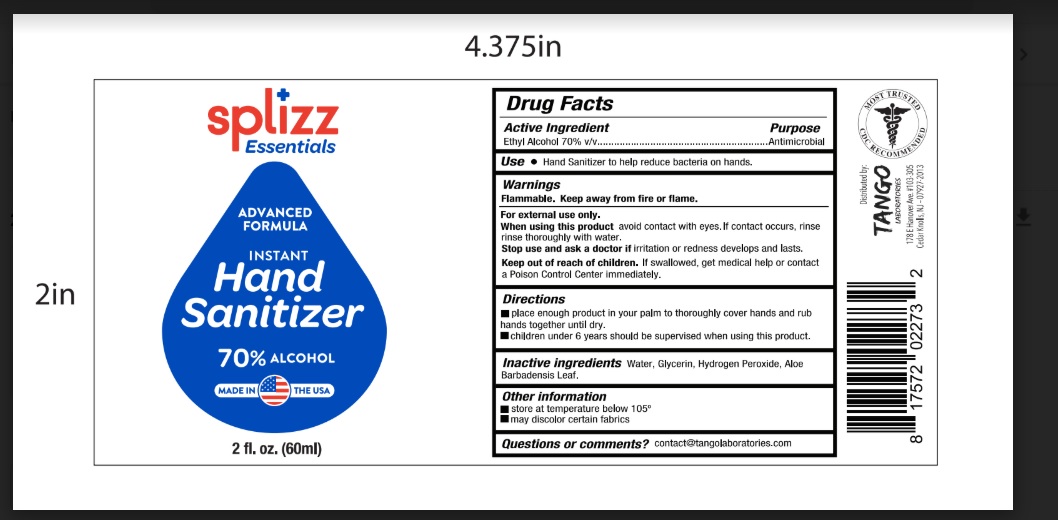 DRUG LABEL: Splizz Essentials
NDC: 77356-716 | Form: LIQUID
Manufacturer: Adonis, LLC.
Category: otc | Type: HUMAN OTC DRUG LABEL
Date: 20200528

ACTIVE INGREDIENTS: ALCOHOL 70 mL/100 mL
INACTIVE INGREDIENTS: GLYCERIN; HYDROGEN PEROXIDE; WATER; ALOE VERA LEAF

Splizz Essentials- Liquid Hand Sanitizer

Active Ingredient(s)

Ethyl Alcohol 70% v/v. .......... Antimicrobial

Purpose

Antimicrobial, Hand Sanitizer

Use

Hand Sanitizer to help reduce bacteria on hands.

Warnings

For external use only. Flammable. Keep away from heat or flame

Do not use

- in children less than 2 months of age
- on open skin wounds

When using this product avoid contact with eyes. If contact occurs, rinse rinse eyes thoroughly with water.

Stop use and ask a doctor if irritation or redness devleops and lasts.

Keep out of reach of children. If swallowed, get medical help or contact a Poison Control Center immediately.

Directions

Place enough product in your palm to thoroughly cover hands and Rub hands together until dry. Supervise children under 6 years should be when using this product.

Other information

- Store at temperature below 105 °
  May discolor certain fabrics

Inactive ingredients

glycerin, hydrogen peroxide, purified water ,Aloe Barbadensis